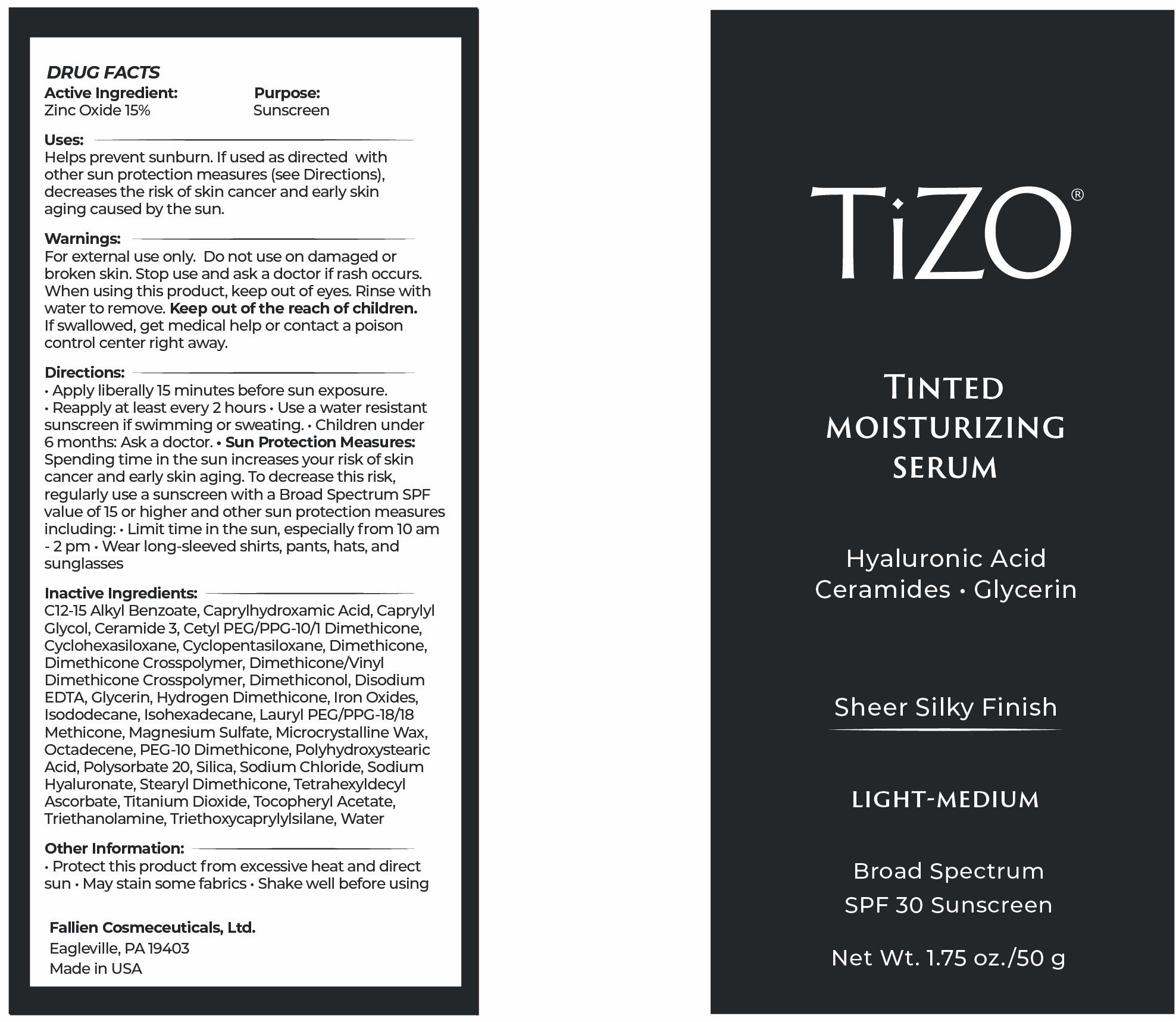 DRUG LABEL: TiZO Tinted Moisturizing Serum - Light-Medium
NDC: 58892-132 | Form: CREAM
Manufacturer: Fallien Cosmeceuticals, Ltd.
Category: otc | Type: HUMAN OTC DRUG LABEL
Date: 20251216

ACTIVE INGREDIENTS: ZINC OXIDE 150 mg/1 g
INACTIVE INGREDIENTS: CI 77499; CI 77492; HYDROGEN DIMETHICONE (20 CST); CYCLOHEXASILOXANE; GLYCERIN; DIMETHICONE; ISOHEXADECANE; DIMETHICONE/VINYL DIMETHICONE CROSSPOLYMER (SOFT PARTICLE); EDETATE DISODIUM ANHYDROUS; POLYSORBATE 20; STEARYL DIMETHICONE (400 MPA.S AT 50C); SILICON DIOXIDE; LAURYL PEG/PPG-18/18 METHICONE; SODIUM HYALURONATE; TETRAHEXYLDECYL ASCORBATE; TRIETHANOLAMINE; TRIETHOXYCAPRYLYLSILANE; CETYL PEG/PPG-10/1 DIMETHICONE (HLB 4); DIMETHICONOL (2000 CST); ISODODECANE; POLYHYDROXYSTEARIC ACID (2300 MW); SODIUM CHLORIDE; WATER; MICROCRYSTALLINE WAX; ALPHA-TOCOPHEROL ACETATE; TITANIUM DIOXIDE; CAPRYLYL GLYCOL; CYCLOPENTASILOXANE; C12-15 ALKYL BENZOATE; CAPRYLHYDROXAMIC ACID; MAGNESIUM SULFATE; OCTADECENE; CI 77491; PEG-10 DIMETHICONE (600 CST); CERAMIDE 3; DIMETHICONE CROSSPOLYMER

Active Ingredient:

Zinc Oxide 15%

Purpose:

Sunscreen

Uses:

Helps prevents sunburn. If used as directed with other sun protection measures (see Directions), decreases the risk of skin cancer and early skin aging caused by the sun.

Warnings:

For external use only. Do not use on damaged or broken skin. Stop use and ask a doctor if rash occurs. When using this product, keep out of eyes. Rinse with water to remove. Keep out of reach of children. If swallowed, get medical help or contact a poison control center right away.

Directions:

Apply liberally 15 minutes before sun exposure. Reapply At least every 2 hours. Use a water resistant product if swimming or sweating. Children under 6 months: Ask a doctor. Sun Protection Measures: Spending time in the sun increases your risk of skin cancer and early skin aging. To decrease this risk, regularly use a sunscreen with a Broad Spectrum SPF value of 15 or higher and other sun protection measures including: Limit time in the sun, especially from 10 a.m. - 2 p.m. Wear long-sleeved shirts, pants, hats, and sunglasses

Inactive Ingredients:

C 12-15 Alkyl Benzoate, Caprylhydroxamic Acid, Caprylyl Glycol, Ceramide 3, CetylPEG/PPG-10/1 Dimethicone, Cyclohexasiloxane, Cyclopentasiloxane, Dimethicone,Dimethicone Crosspolymer, Dimethicone/Vinyl Dimethicone Crosspolymer, Dimethiconol, Disodium EDTA, Glycerin, Hydrogen Dimethicone, Iron Oxides, Isododecane, Isohexadecane, Lauryl PEG/PPG-18/18 Methicone, Magnesium Sulfate, Microcrystalline Wax, Octadecene, PEG-10 Dimethicone, Polyhydroxystearic Acid, Polysorbate 20, Silica, Sodium Chloride, Sodium Hyaluronate, Stearyl Dimethicone, Tetrahexyldecyl Ascorbate, Titanium Dioxide,
Tocopheryl Acetate, Triethanolamine, Triethoxycaprylylsilane, Water

Other Information:

Protect this product from excessive heat and direct sun. May stain some fabrics. Shake well before using.

Warnings:

Keep out of the reach of children.